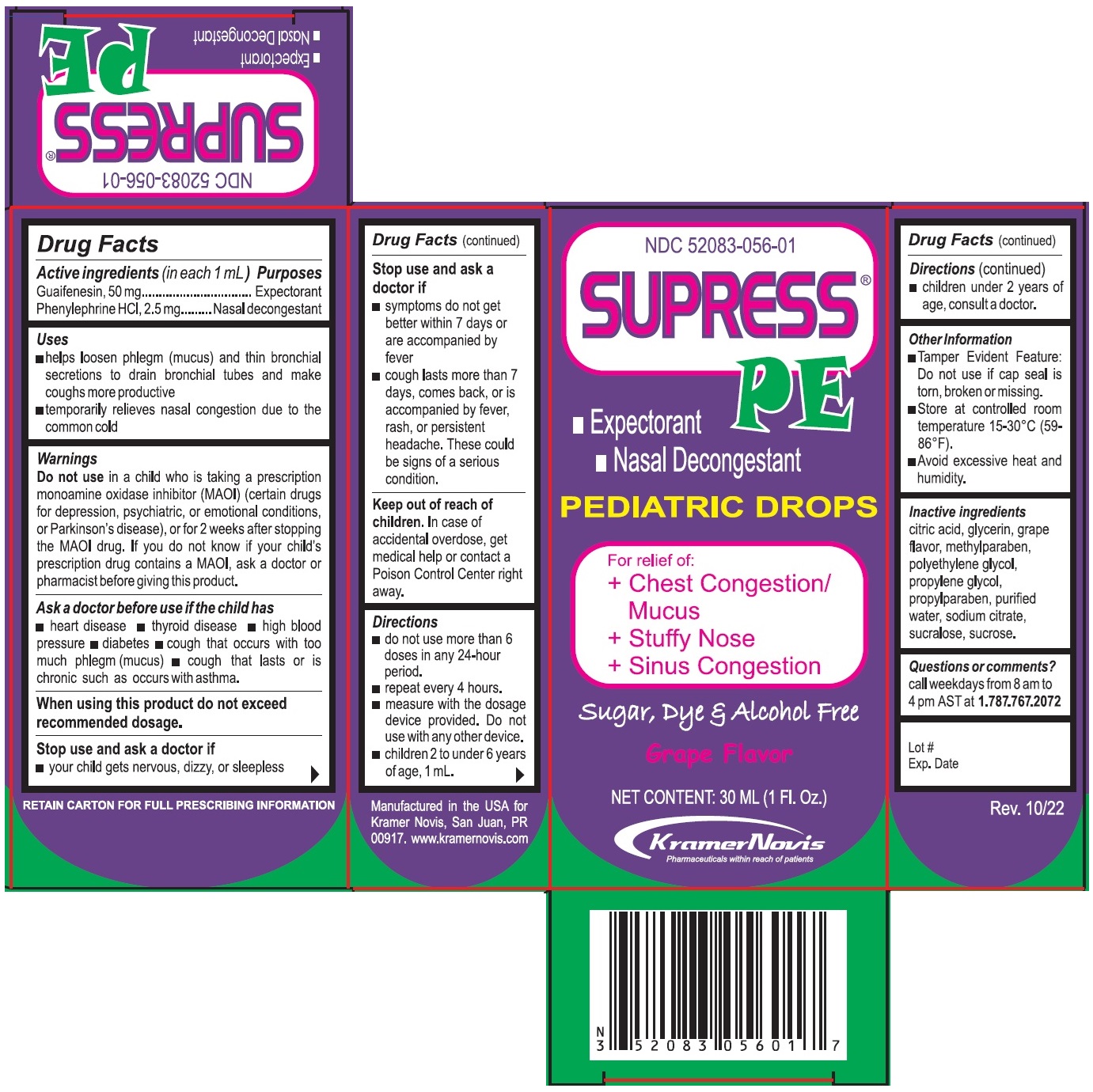 DRUG LABEL: SUPRESS-PE
NDC: 52083-056 | Form: SOLUTION/ DROPS
Manufacturer: Kramer Novis
Category: otc | Type: HUMAN OTC DRUG LABEL
Date: 20250326

ACTIVE INGREDIENTS: GUAIFENESIN 50 mg/1 mL; PHENYLEPHRINE HYDROCHLORIDE 2.5 mg/1 mL
INACTIVE INGREDIENTS: CITRIC ACID MONOHYDRATE; GLYCERIN; METHYLPARABEN; POLYETHYLENE GLYCOL, UNSPECIFIED; PROPYLENE GLYCOL; PROPYLPARABEN; WATER; SODIUM CITRATE, UNSPECIFIED FORM; SUCRALOSE; SUCROSE

SUPRESS® PE PEDIATRIC DROPS

Active ingredients (in each 1 mL)

Guaifenesin, 50 mg
Phenylephrine HCl, 2.5 mg

Purposes

Expectorant
Nasal decongestant

Uses

• helps loosen phlegm (mucus) and thin bronchial secretions to drain bronchial tubes and make coughs more productive
• temporarily relieves nasal congestion due to the common cold

Warnings

Do not use in a child who is taking a prescription monoamine oxidase inhibitor (MAOI) (certain drugs for depression, psychiatric, or emotional conditions, or Parkinson’s disease), or for 2 weeks after stopping the MAOI drug. If you do not know if your child's prescription drug contains a MAOI, ask a doctor or pharmacist before giving this product.

Ask a doctor before use if the child has
• heart disease • thyroid disease • high blood pressure • diabetes • cough that occurs with too much phlegm (mucus) • cough that lasts or is chronic such as occurs with asthma.

When using this product do not exceed recommended dosage.

Stop use and ask a doctor if
• your child gets nervous, dizzy, or sleepless
• symptoms do not get better within 7 days or are accompanied by fever
• cough lasts more than 7 days, comes back, or is accompanied by fever, rash or persistent headache. These could be signs of a serious condition.

Keep out of reach of children. In case of accidental overdose, get medical help or contact a Poison Control Center right away.

Directions

• do not use more than 6 doses in any 24-hour period.
• repeat every 4 hours.
• measure with the dosage device provided. Do not use with any other device.
• children 2 to under 6 years of age, 1 mL.
• children under 2 years of age, consult a doctor.

Other Information

• Tamper Evident Feature: Do not use if cap seal is torn, broken or missing.
• Store at controlled room temperature 15-30°C (59-86°F).
• Avoid excessive heat and humidity.

Inactive ingredients

Citric acid, glycerin, grape flavor, methylparaben, polyethylene glycol, propylene glycol, propylparaben, purified water, sodium citrate, sucralose, sucrose.

Questions or comments?

call weekdays from 8 am to 4 pm AST at 1.787.767.2072

PEDIATRIC DROPS

For Relief of:
+ Chest Congestion/Mucus
+ Stuffy Nose
+ Sinus Congestion

Sugar, Dye & Alcohol Free

Grape Flavor

RETAIN CARTON FOR FULL PRESCRIBING INFORMATION

Manufactured in the USA for Kramer Novis, San Juan, PR 00917. www.kramernovis.com